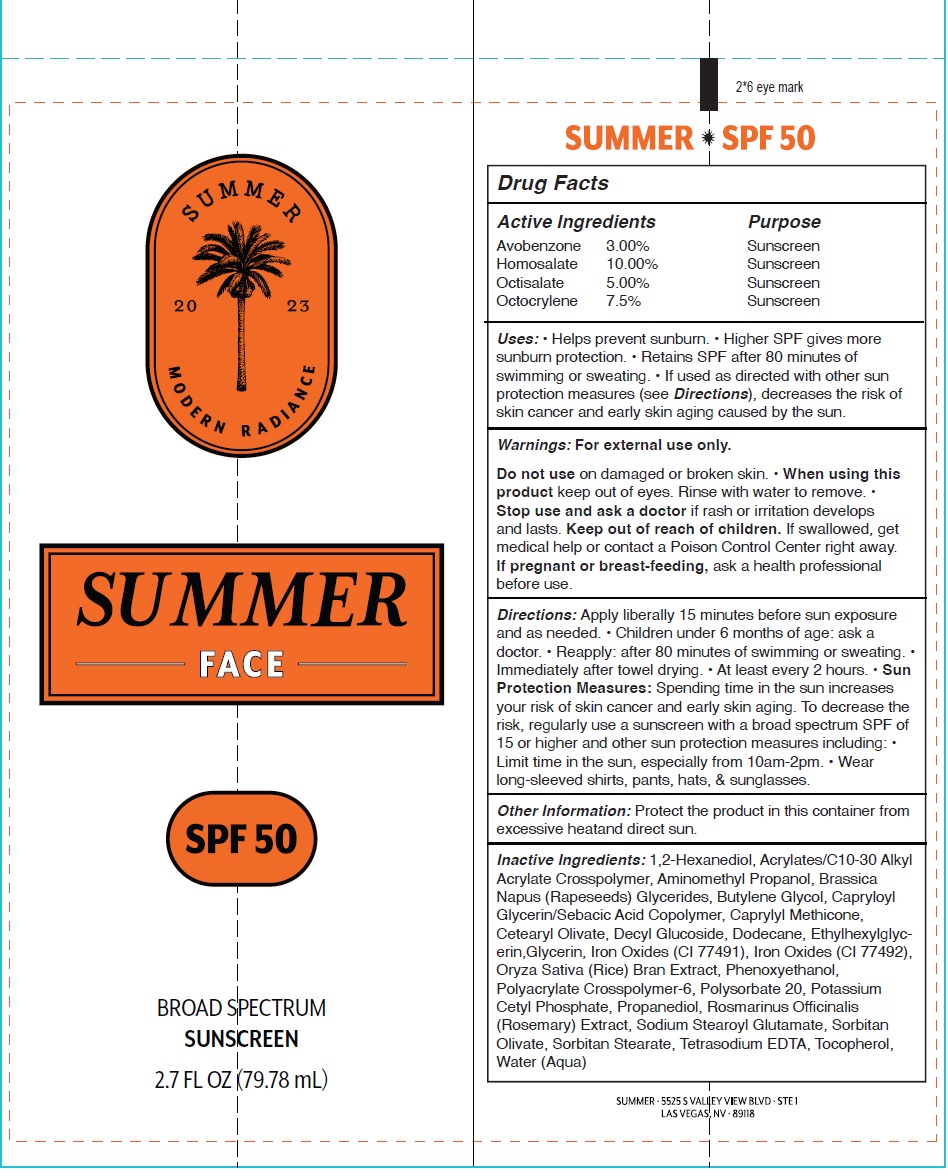 DRUG LABEL: Summer Face Sunscreen SPF 50
NDC: 84281-893 | Form: LIQUID
Manufacturer: SUMMER GELEE LLC
Category: otc | Type: HUMAN OTC DRUG LABEL
Date: 20251006

ACTIVE INGREDIENTS: AVOBENZONE 30 mg/1 mL; HOMOSALATE 100 mg/1 mL; OCTISALATE 50 mg/1 mL; OCTOCRYLENE 75 mg/1 mL
INACTIVE INGREDIENTS: 1,2-HEXANEDIOL; AMINOMETHYLPROPANOL; BUTYLENE GLYCOL; CAPRYLYL TRISILOXANE; CETEARYL OLIVATE; DECYL GLUCOSIDE; DODECANE; ETHYLHEXYLGLYCERIN; GLYCERIN; FERRIC OXIDE RED; FERRIC OXIDE YELLOW; RICE BRAN; PHENOXYETHANOL; AMMONIUM ACRYLOYLDIMETHYLTAURATE, DIMETHYLACRYLAMIDE, LAURYL METHACRYLATE AND LAURETH-4 METHACRYLATE COPOLYMER, TRIMETHYLOLPROPANE TRIACRYLATE CROSSLINKED (45000 MPA.S); POLYSORBATE 20; POTASSIUM CETYL PHOSPHATE; PROPANEDIOL; ROSEMARY; SODIUM STEAROYL GLUTAMATE; SORBITAN OLIVATE; SORBITAN STEARATE; TETRASODIUM EDTA; TOCOPHEROL; WATER

Summer Face Sunscreen SPF 50

Active Ingredients

Avobenzone 3.00%
Homosalate 10.00%
Octisalate 5.00%
Octocrylene 7.5%

Purpose

Sunscreen

Uses:

• Helps prevent sunburn. • Higher SPF gives moresunburn protection. • Retains SPF after 80 minutes of swimming or sweating. • If used as directed with other sun protection measures (see Directions), decreases the risk of skin cancer and early skin aging caused by the sun.

Warnings:

For external use only.

Do not use

on damaged or broken skin.

When using this product

keep out of eyes. Rinse with water to remove.

Stop use and ask a doctor

- if rash or irritation develops and lasts.

Keep out of reach of children.

If swallowed, get medical help or contact a Poison Control Center right away.

If pregnant or breast-feeding,

ask a health professional before use.

Directions:

Apply liberally 15 minutes before sun exposure and as needed. • Children under 6 months of age: ask a doctor. • Reapply: after 80 minutes of swimming or sweating. • Immediately after towel drying. • At least every 2 hours. • Sun Protection Measures:Spending time in the sun increases your risk of skin cancer and early skin aging. To decrease the risk, regularly use a sunscreen with a broad spectrum SPF of 15 or higher and other sun protection measures including: • Limit time in the sun, especially from 10am-2pm. • Wear long-sleeved shirts, pants, hats, & sunglasses.

Other Information:

Protect the product in this container from excessive heatand direct sun.

Inactive Ingredients:

1,2-Hexanediol, Acrylates/C10-30 Alkyl Acrylate Crosspolymer, Aminomethyl Propanol, Brassica Napus (Rapeseeds) Glycerides, Butylene Glycol, Capryloyl Glycerin/Sebacic Acid Copolymer, Caprylyl Methicone, Cetearyl Olivate, Decyl Glucoside, Dodecane, Ethylhexylglycerin, Glycerin, Iron Oxides (CI 77491), Iron Oxides (CI 77492), Oryza Sativa (Rice) Bran Extract, Phenoxyethanol, Polyacrylate Crosspolymer-6, Polysorbate 20, Potassium Cetyl Phosphate, Propanediol, Rosmarinus Officinalis (Rosemary) Extract, Sodium Stearoyl Glutamate, Sorbitan Olivate, Sorbitan Stearate, Tetrasodium EDTA, Tocopherol, Water (Aqua)